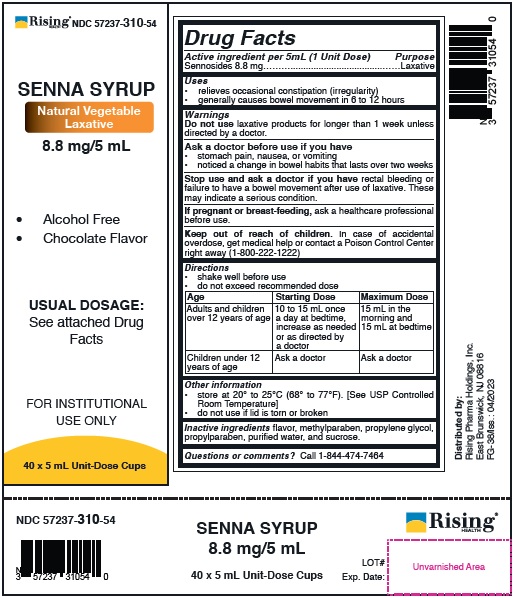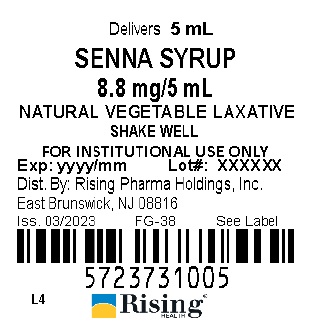 DRUG LABEL: Senna Syrup
NDC: 57237-310 | Form: LIQUID
Manufacturer: Rising Pharma Holdings, Inc.
Category: otc | Type: HUMAN OTC DRUG LABEL
Date: 20250701

ACTIVE INGREDIENTS: SENNOSIDES 8.8 mg/5 mL
INACTIVE INGREDIENTS: METHYLPARABEN; PROPYLENE GLYCOL; PROPYLPARABEN; WATER; SUCROSE

ACTIVE INGREDIENT

Senna Syrup (8.8 mg/5 mL)

Active ingredient per 5 mL(1 Unit Dose) Sennosides 8.8 mg

Drug Facts

Purpose

Laxative

Uses

- relieves occasional constipation (irregularity)
- generally causes bowel movement in 6 to 12 hours

Warnings

Do not use laxative products for longer than 1 week unless directed by a doctor.

Ask a doctor before use if you have

- stomach pain, nausea, or vomiting
- noticed a change in bowel habits that lasts over two weeks

Stop use and ask a doctor if you have rectal bleeding or failure to have a bowel movement after use of laxative. These may indicate a serious condition.

PREGNANCY

If pregnant or breast-feeding, ask a healthcare professional before use.

Keep out of reach of children. In case of accidental overdose, get medical help or contact a Poison Control Center right away (1-800-222-1222)

Directions

- shake well before use
- do not exceed recommended dose

Age | Starting Dose | Maximum Dose
Adults and children over 12 years of age | 10 to 15 mL once a day at bedtime, increase as needed or as directed by a doctor | 15 mL in the morning and 15 mL at bedtime
Children under 12 years of age | Ask a doctor | Ask a doctor

Other information

• store at 20° to 25°C (68° to 77°F). [See USP Controlled Room Temperature]
• do not use if lid is torn or broken

INACTIVE INGREDIENT

Inactive ingredients flavor, methylparaben, propylene glycol, propylparaben, purified water, and sucrose.

Questions or comments? Call 1-844-474-7464

PACKAGE LABEL

Distributed by:

Rising Pharma Holdings, Inc.

East Brunswick, NJ 08816

FG-38/Iss.: 04/2023

Lid Label

Case Label